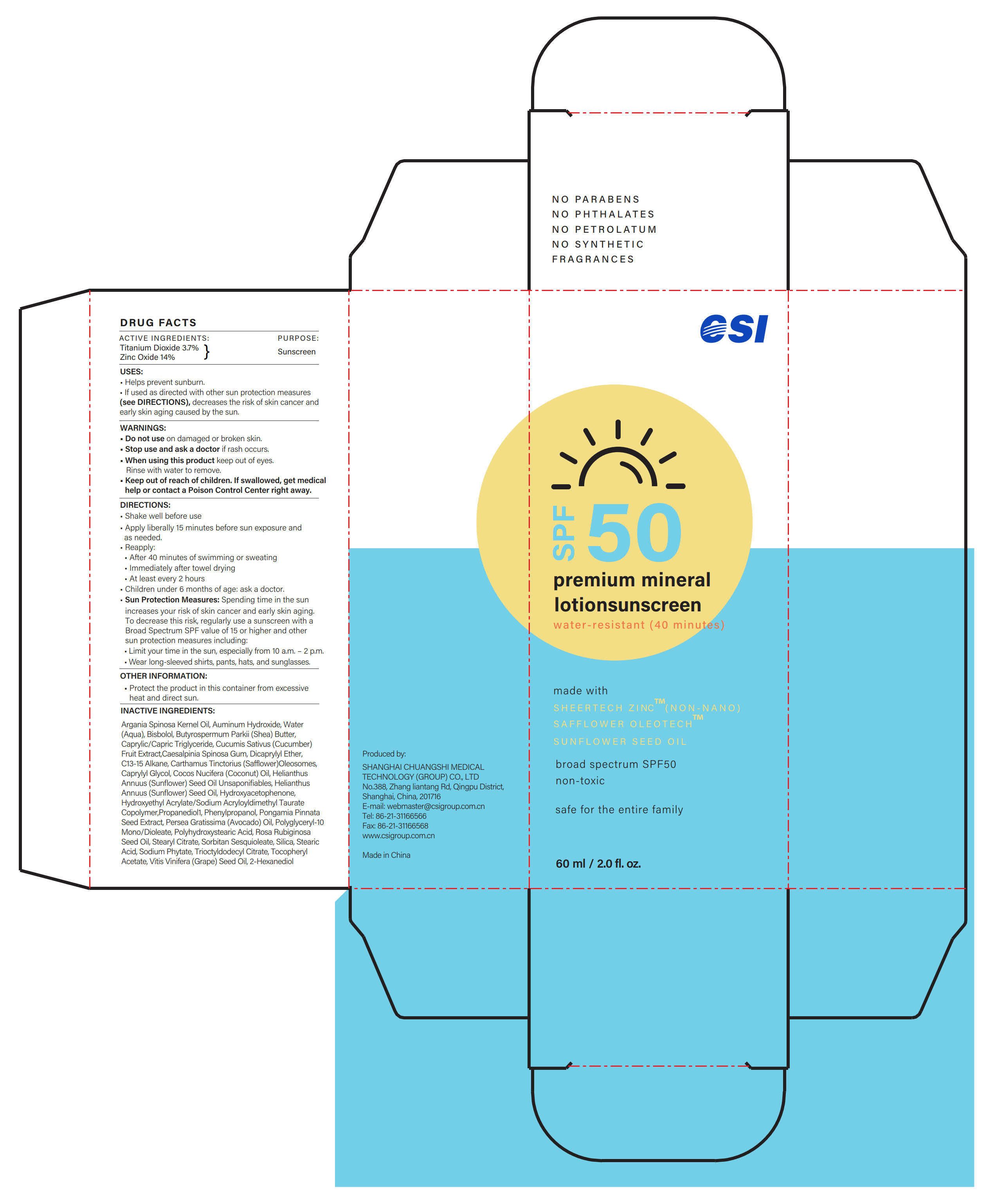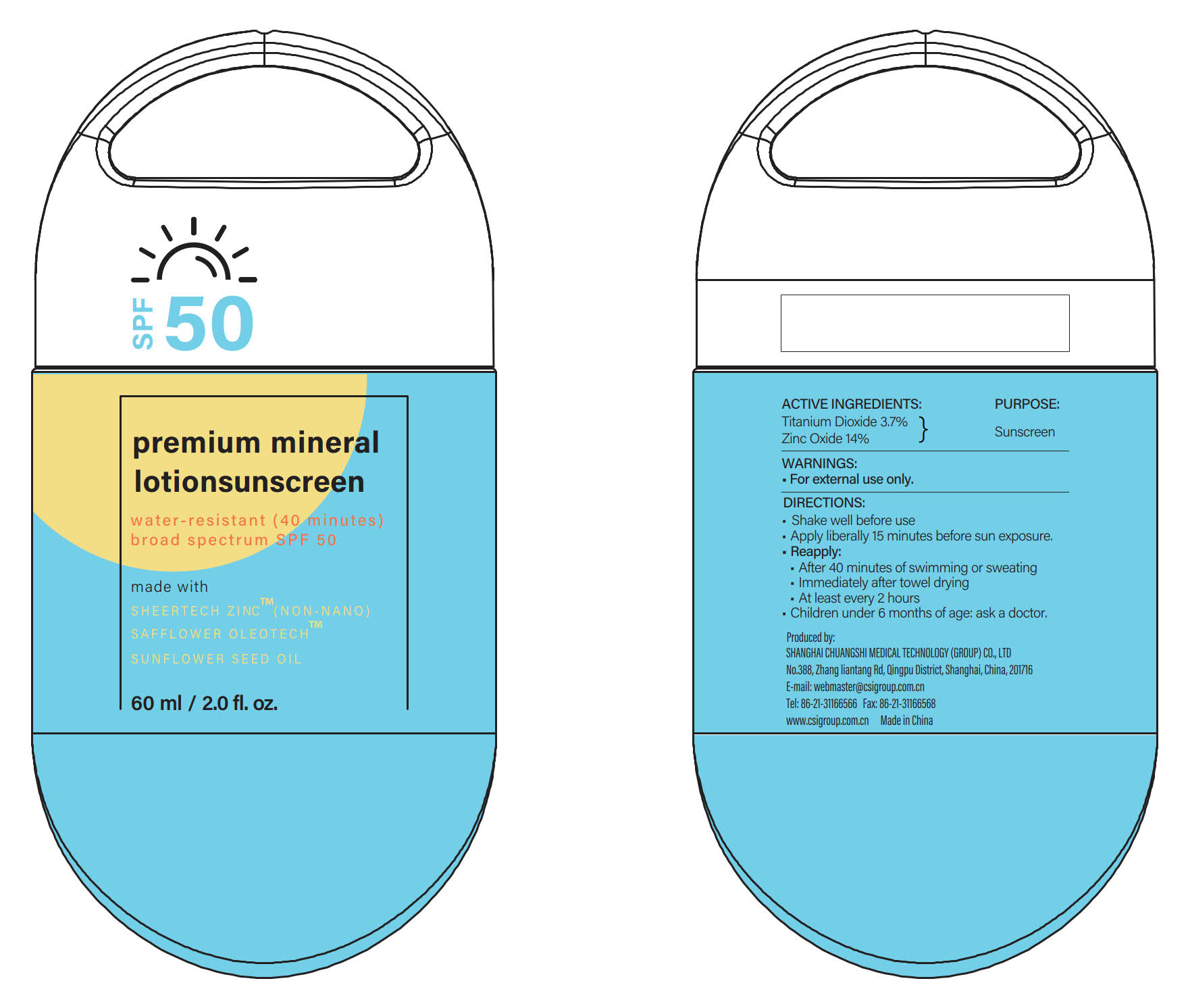 DRUG LABEL: Sunscreen-Lotion
NDC: 73557-575 | Form: LOTION
Manufacturer: Shanghai Chuangshi Medical Technology (Group) Co., Ltd.
Category: otc | Type: HUMAN OTC DRUG LABEL
Date: 20240320

ACTIVE INGREDIENTS: TITANIUM DIOXIDE 0.037 g/1 g; ZINC OXIDE 0.14 g/1 g
INACTIVE INGREDIENTS: DICAPRYLYL ETHER; CARTHAMUS TINCTORIUS (SAFFLOWER) OLEOSOMES; C13-15 ALKANE; HYDROXYACETOPHENONE; PHYTATE SODIUM; ALUMINUM HYDROXIDE; MONOSTEARYL CITRATE; HYDROXYETHYL ACRYLATE/SODIUM ACRYLOYLDIMETHYL TAURATE COPOLYMER (45000 MPA.S AT 1%); SORBITAN SESQUIOLEATE; TRIOCTYLDODECYL CITRATE; PHENYLPROPANOL; SHEA BUTTER; MEDIUM-CHAIN TRIGLYCERIDES; STEARIC ACID; LEVOMENOL; ALPHA-TOCOPHEROL ACETATE; SUNFLOWER OIL; POLYHYDROXYSTEARIC ACID (2300 MW); 1,2-HEXANEDIOL; POLYGLYCERYL-10 DIOLEATE; PONGAMIA PINNATA SEED; WATER; AVOCADO OIL; CUCUMBER; CAESALPINIA SPINOSA RESIN; ROSA RUBIGINOSA SEED OIL; GRAPE SEED OIL; COCONUT OIL; PROPANEDIOL; SILICON DIOXIDE; CAPRYLYL GLYCOL; ARGAN OIL

CSI, Sunscreen-Lotion, Zinc Oxide & Titanium Dioxide, 60 mL

ACTIVE INGREDIENTS

Titanium Dioxide 3.7% ...... Purpose: Sunscreen

Zinc Oxide 14% ...... Purpose: Sunscreen

PURPOSE

Sunscreen

USES

- Helps prevent sunburn.
- If used as directed with other sun protection measures (see DIRECTIONS), decreases the risk of skin cancer and early skin aging caused by the sun.

WARNINGS

(See following 5 SECTIONs)

Do not use

on damaged or broken skin.

Stop use...

if rash occurs.

When using this product

keep out of eyes.

Rinse with water to remove.

... Ask a doctor

if rash occurs.

Keep out of reach of children

If swallowed, get medical help or contact a Poison Control Center right away.

DIRECTIONS

- Shake well before use
- Apply liberally 15 minutes before sun exposure and as needed.
- Reapply:

·After 40 minutes of swimming or sweating

·Immediately after towel drying

·At least every 2 hours

- Children under 6 months of age: ask a doctor.
- Sun Protection Measures: Spending time in the sun increases your risk of skin cancer and early skin aging. To decrease this risk, regularly use a sunscreen with a Broad Spectrum SPF value of 15 or higher and other sun protection measures including:

·Limit your time in the sun, especially from 10 a.m. - 2 p.m.

·Wear long-sleeved shirts, pants, hats, and sunglasses.

OTHER INFORMATION

- Protect the product in the container from excessive heat and direct sun.

INACTIVE INGREDIENTS

Argania Spinosa Kernel Oil, Auminum Hydroxide, Water (Aqua), Bisbolol, Butyrospermum Parkii (Shea) Butter, Caprylic/Capric Triglyceride, Cucumis Sativus (Cucumber) Fruit Extract, Caesalpinia Spinosa Gum, Dicaprylyl Ether, C13-15 Alkane, Carthamus Tinctorius (Safflower) Oleosomes, Caprylyl Glycol, Cocos Nucifera (Coconut) Oil, Helianthus Annuus (Sunflower) Seed Oil Unsaponifiables, Helianthus Annuus (Sunflower) Seed Oil, Hydroxyacetophenone, Hydroxyethyl Acrylate/Sodium Acryloyldimethyl Taurate Copolymer, Propanediol, Phenylpropanol, Pongamia Pinnata Seed Extract, Persea Gratissima (Avocado) Oil, Polyglyceryl-10 Mono/Dioleate, Polyhydroxystearic Acid, Rosa Rubiginosa Seed Oil, Stearyl Citrate, Sorbitan Sesquioleate, Silica, Stearic Acid, Sodium Phytate, Trioctyldodecyl Citrate, Tocopheryl Acetate, Vitis Vinifera (Grape) Seed Oil, 2-Hexanediol

QUESTIONS

E-mail: webmaster@csigroup.com.cn

Tel: 86-21-31166566

Fax: 86-21-31166568

www.csigroup.com.cn